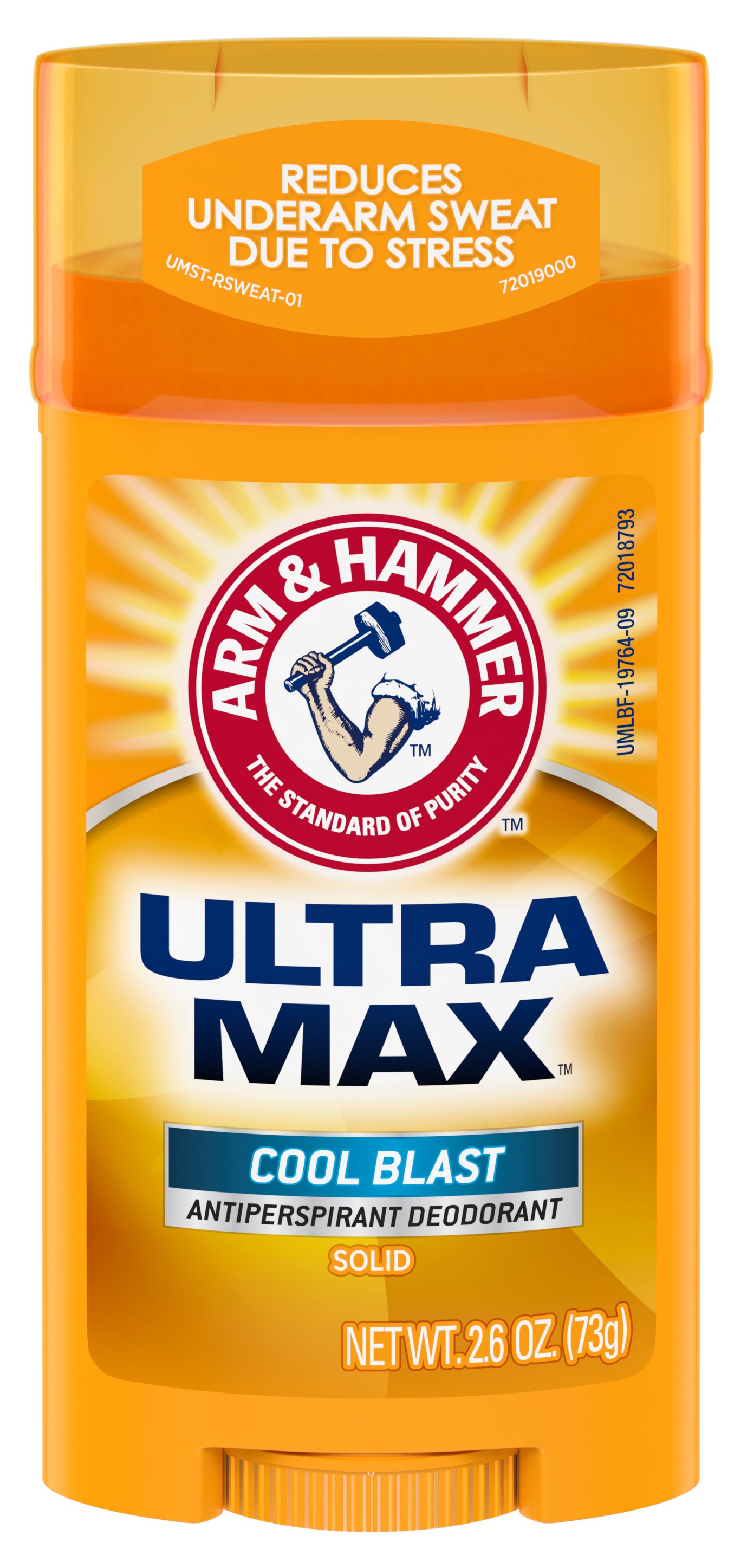 DRUG LABEL: UltraMax Invisible Solid - Cool Blast
NDC: 10237-872 | Form: STICK
Manufacturer: Church & Dwight Co., Inc.
Category: otc | Type: HUMAN OTC DRUG LABEL
Date: 20251205

ACTIVE INGREDIENTS: ALUMINUM CHLOROHYDRATE 0.19 g/1 g
INACTIVE INGREDIENTS: C12-20 ALKYL BENZOATE; CYCLOMETHICONE 5; PPG-14 BUTYL ETHER; STEARYL ALCOHOL; HYDROGENATED CASTOR OIL; TALC; PETROLATUM; SODIUM BICARBONATE; STARCH, CORN; XANTHAN GUM; MALTODEXTRIN

Arm and Hammer UltraMax Invisible Solid - Cool Blast

ACTIVE INGREDIENT

Aluminum Chlorohydrate 19%

PURPOSE

Antiperspirant

INDICATIONS AND USAGE

Use reduces underarm perspiration

WARNINGS

For external use only

Do not use on broken skin

Stop use if rash or irritation occurs

Ask a doctor before use if you have kidney disease

Keep out of reach of children. If swallowed, get medical help or contact a Poison Control Center right away.

Directions

Apply a thin layer to underarms only

INACTIVE INGREDIENT

PPG-14 Butyl Ether, Cyclopentasiloxane, Stearyl Alcohol, Talc, Hydrogenated Castor Oil, Petrolatum, Fragrance, Sodium Bicarbonate (Baking Soda), Corn Starch Modified, Polysaccharides, Maltodextrin.

Questions or Comments?

Call 1-800-248-8820

M-F 9am-5pm ET

or visit www.ahultramax.com

PACKAGE LABEL

REDUCES

UNDERARM SWEAT

DUE TO STRESS

ARM & HAMMER

THE STANDARD OF PURITY

ULTRA MAX

COOL BLAST

ANTIPERSPIRANT DEODORANT

SOLID

NET WT. 2.6 OZ. (73g)